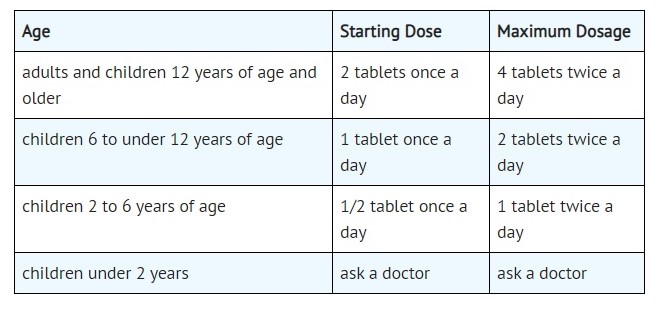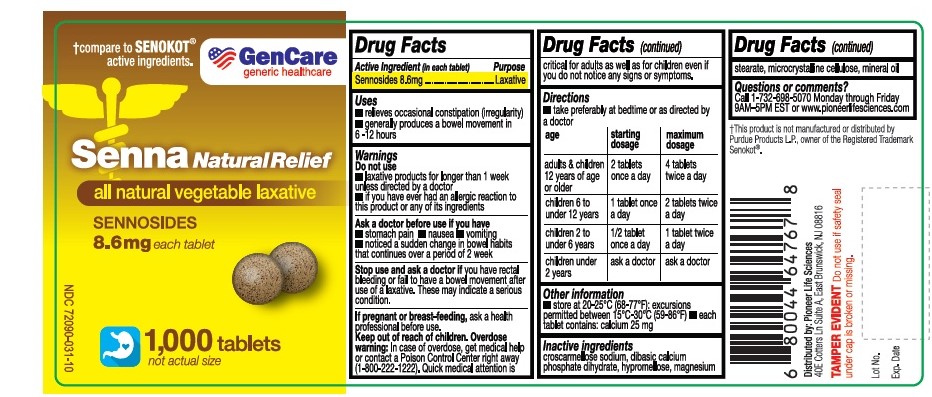 DRUG LABEL: Senna Natural Relief
NDC: 72090-031 | Form: TABLET
Manufacturer: Pioneer Life Sciences, LLC
Category: otc | Type: HUMAN OTC DRUG LABEL
Date: 20200810

ACTIVE INGREDIENTS: SENNOSIDES 8.6 mg/1 1
INACTIVE INGREDIENTS: SODIUM LAURYL SULFATE; MICROCRYSTALLINE CELLULOSE; SILICON DIOXIDE; STEARIC ACID D7; PARAFFIN; DIBASIC CALCIUM PHOSPHATE DIHYDRATE; HYPROMELLOSES; MAGNESIUM STEARATE; MALTODEXTRIN; CROSCARMELLOSE SODIUM

Active Ingredient

Sennosides 8.6 mg

Purpose

Laxative

Uses:

relieves occasional constipation (irregularity).
generally causes bowel movement within 6 to 12 hours.

Warnings:

Do not use -

Laxative products for longer than 1 week, unless directed by a doctor.

If you have ever had an allergic reaction to this product or any of its ingredients.

Ask Doctor:

Ask a doctor before use if you have - Stomach pain, nausea, vomiting, a sudden change in bowel movements that persists over 2 weeks

ASK DOCTOR/PHARMACIST:

Stop use and ask a doctor if you have:

Rectal bleeding or fail to have a bowel movement after use of a laxative.

These could be signs of a serious condition.

PREGNANCY

If pregnant or breast-feeding, ask a health professional before use.

Keep out of reach of children. In case of overdose, get medical help or contact a Poison Control Center (1-800-222-1222), Quick medical attention is critical for adults as well as for children even if you do not notice any signs or symptoms.

DIRECTIONS

Take preferably at bedtime or as directed by a doctor.

OTHER INFORMATION

store at 20-25°C (68-77°F) excursions permitted between15°-30°C (59°-86°F)

each tablet contains: Calcium 25 mg & sodium 3 mg

INACTIVE INGREDIENTS

Colloidal silicon dioxide,croscarmellose sodium, Dicalcium phosphate, Hypromellose, liquid paraffin, magnesium stearate, microcrystalline cellulose, Maltodextrin, Purified water, Sodium lauryl sulphate, Stearic Acid.

QUESTIONS OR COMMENTS?

Call 1-732-698-5070 Monday through Friday 9AM–5PM EST or www.pioneerlifesciences.com